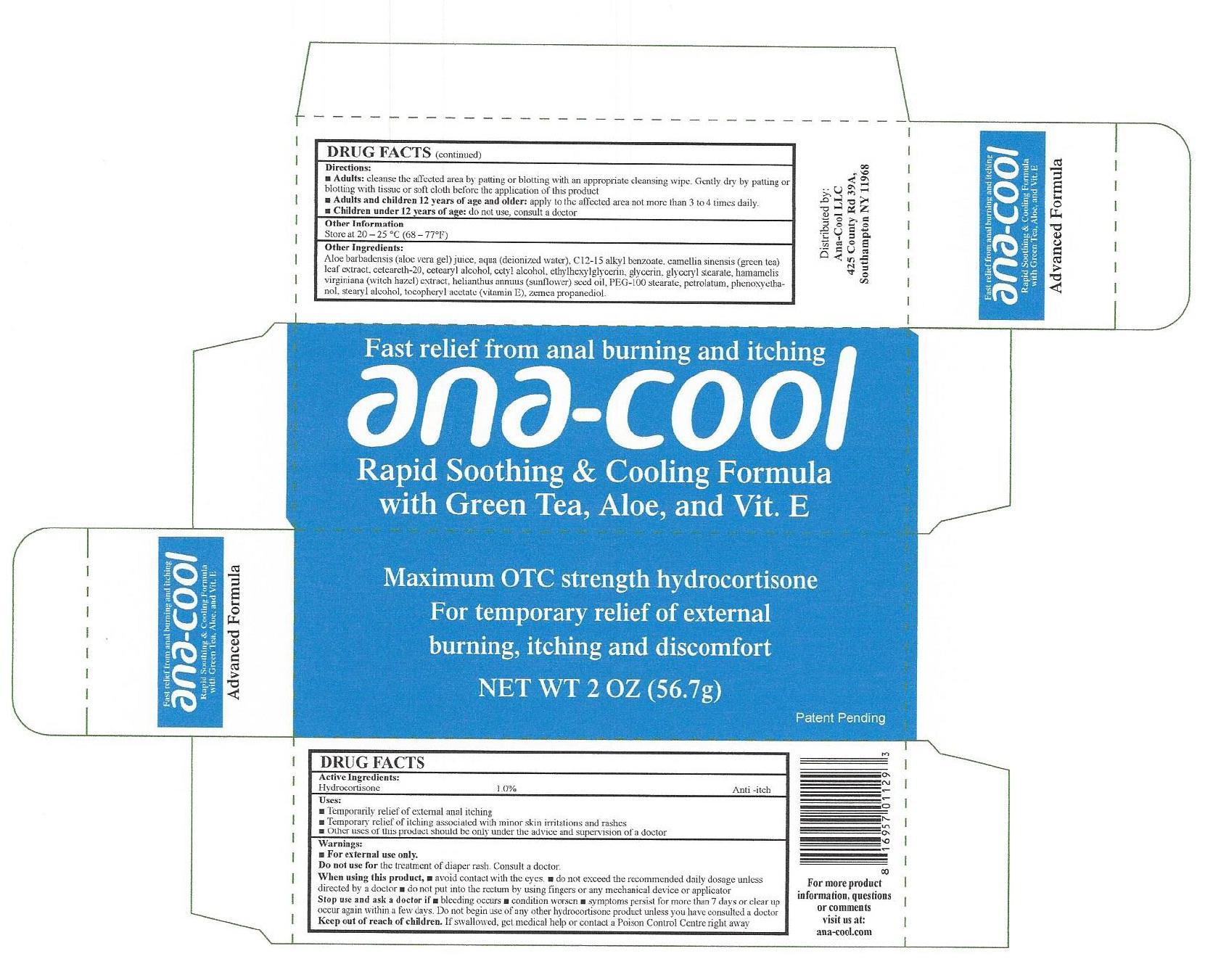 DRUG LABEL: Ana Cool Rapid Soothing Cooling Formula
NDC: 70288-714 | Form: CREAM
Manufacturer: Ana-Cool, LLC
Category: otc | Type: HUMAN OTC DRUG LABEL
Date: 20231105

ACTIVE INGREDIENTS: HYDROCORTISONE 10 mg/1 g
INACTIVE INGREDIENTS: WATER; ALKYL (C12-15) BENZOATE; GREEN TEA LEAF; CETOSTEARYL ALCOHOL; CETYL ALCOHOL; ETHYLHEXYLGLYCERIN; GLYCERIN; GLYCERYL MONOSTEARATE; HAMAMELIS VIRGINIANA TOP; SUNFLOWER OIL; ALOE VERA LEAF; PEG-100 STEARATE; PETROLATUM; PHENOXYETHANOL; STEARYL ALCOHOL; .ALPHA.-TOCOPHEROL ACETATE

Ana-Cool Rapid Soothing & Cooling Formula

Active Ingredients:

Hydrocortisone 1.0%

PURPOSE

Anti -itch

Uses:

- Temporarily relief of external anal itching
- Temporary relief of itching associated with minor skin irritations and rashes
- Other uses of this product should be only under the advice and supervision of a doctor

Warnings:

- For external use only.

Do not use for

the treatment of diaper rash. Consult a doctor.

When using this product,

• avoid contact with the eyes • do not exceed the recommended daily dosage unless directed by a doctor • do not put into the rectum by using fingers or any mechanical device or applicator

Stop use and ask a doctor if

• bleeding occurs • condition worsen • symptoms persist for more than 7 days or clear up occur again within a few days. Do not begin use of any other hydrocortisone product unless you have consulted a doctor

Keep out of reach of children.

If swallowed, get medical help or contact a Poison Control Centre right away

Directions:

- cleanse the affected area by patting or blotting with an appropriate cleansing wipe. Gently dry by patting or blotting with tissue or soft cloth before the applicationof this product Adults:
- apply to the affected area not more than 3 to 4 times daily. Adults and children 12 years of age and older:
- do not use, consult a doctor Children under 12 years of age:

Other Information

Store at 20 - 25 °C (68-77°F)

Other Ingredients:

Aloe barbadensis (aloe vera gel) juice, aqua (deionized water), C12-15 alkyl benzoate, camellia sinensis (green tea) leaf extract, cetearcth-20, cetearyl alcohol, cetyl alcohol, ethylhexylglycerin, glycerin, glyceryl stearate, hamamelis virginiana (witch hazel) extract, helianthus annuus (sunflower) seed oil, PEG-100 stearate, petrolatum, phenoxyethanol, stearyl alcohol, tocopheryl acetate (vitamin E), zemea propanediol.